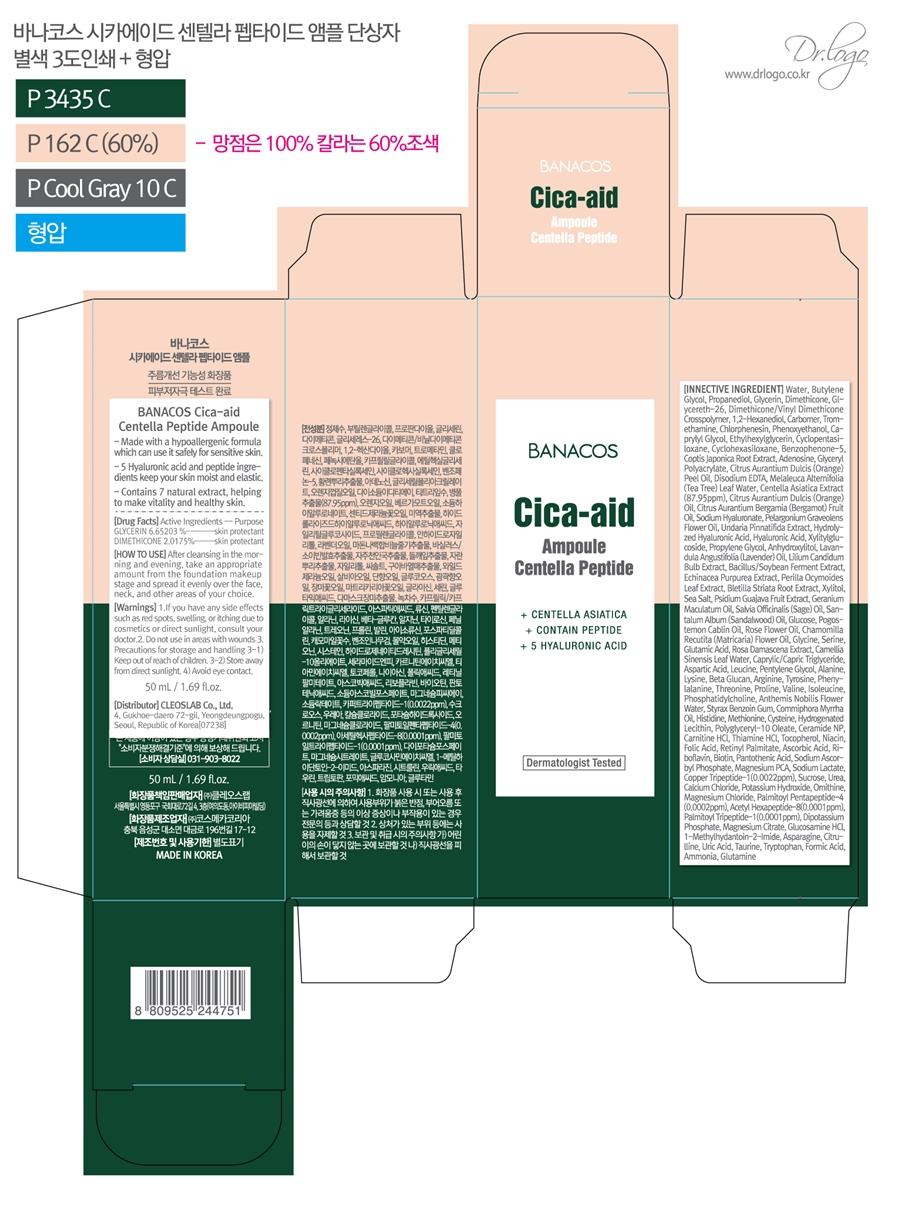 DRUG LABEL: BANACOS Cica-aid Centella Peptide ampoule
NDC: 79540-304 | Form: LIQUID
Manufacturer: Cleoslab Co.,Ltd
Category: otc | Type: HUMAN OTC DRUG LABEL
Date: 20211219

ACTIVE INGREDIENTS: DIMETHICONE 2.0175 g/100 mL; GLYCERIN 6.65203 g/100 mL
INACTIVE INGREDIENTS: ROSA CENTIFOLIA FLOWER 0.0003125 mL/100 mL; CHLORPHENESIN 0.2 mL/100 mL; PHOSPHATIDYLCHOLINE, SOYBEAN 0.000025 mL/100 mL; LEUCINE 0.00006900744 mL/100 mL; PROLINE 0.00003003996 mL/100 mL; CHAMAEMELUM NOBILE FLOWER OIL 0.00002 mL/100 mL; SOYBEAN 0.00175 mL/100 mL; ROSA DAMASCENA FLOWER 0.0001 mL/100 mL; SODIUM ASCORBYL PHOSPHATE 0.0000004 mL/100 mL; ASCORBIC ACID 0.000001 mL/100 mL; RIBOFLAVIN 0.000001 mL/100 mL; BIOTIN 0.000001 mL/100 mL; SUCROSE 0.0000000838 mL/100 mL; UREA 0.00000007 mL/100 mL; CALCIUM CHLORIDE 0.0000000538 mL/100 mL; POTASSIUM HYDROXIDE 0.0000000512 mL/100 mL; MAGNESIUM CHLORIDE 0.0000000234 mL/100 mL; PALMITOYL PENTAPEPTIDE-4 0.00000002 mL/100 mL; PALMITOYL TRIPEPTIDE-1 0.00000001 mL/100 mL; XYLITYLGLUCOSIDE 0.004 mL/100 mL; GUAVA 0.001 mL/100 mL; GERANIUM MACULATUM ROOT OIL 0.000625 mL/100 mL; ANHYDROUS DEXTROSE 0.0004 mL/100 mL; CAPRYLYL GLYCOL 0.100025 mL/100 mL; ETHYLHEXYLGLYCERIN 0.100015 mL/100 mL; PREZATIDE COPPER 0.00000022 mL/100 mL; HYALURONIC ACID 0.005 mL/100 mL; ISOLEUCINE 0.0000270064 mL/100 mL; ARGININE 0.0000380354 mL/100 mL; TYROSINE 0.00003400692 mL/100 mL; PHENYLALANINE 0.00003200552 mL/100 mL; STYRAX BENZOIN RESIN 0.00001875 mL/100 mL; MYRRH OIL 0.00001625 mL/100 mL; THREONINE 0.00003005052 mL/100 mL; VALINE 0.00003001348 mL/100 mL; MAGNESIUM PIDOLATE 0.0000002628 mL/100 mL; ORNITHINE 0.00000005 mL/100 mL; MAGNESIUM CITRATE 0.0000000062 mL/100 mL; GLUCOSAMINE HYDROCHLORIDE 0.000000006 mL/100 mL; ASPARAGINE 0.00000000472 mL/100 mL; CITRULLINE 0.00000000456 mL/100 mL; URIC ACID 0.000000004 mL/100 mL; TAURINE 0.0000000024 mL/100 mL; GLUTAMINE 0.0000000008 mL/100 mL; TEA TREE OIL 0.0094 mL/100 mL; BENZOPHENONE-5 0.05 mL/100 mL; METHIONINE 0.0000115028 mL/100 mL; FOLIC ACID 0.000001 mL/100 mL; VITAMIN A PALMITATE 0.000001 mL/100 mL; MEDIUM-CHAIN TRIGLYCERIDES 0.000095 mL/100 mL; GLYCERETH-26 2 mL/100 mL; PHENOXYETHANOL 0.2 mL/100 mL; FORMIC ACID 0.0000000012 mL/100 mL; ADENOSINE 0.04 mL/100 mL; CENTELLA ASIATICA WHOLE 0.008795 mL/100 mL; BERGAMOT OIL 0.0068125 mL/100 mL; UNDARIA PINNATIFIDA 0.005 mL/100 mL; SEA SALT 0.0010000482 mL/100 mL; GLYCINE 0.0002453688 mL/100 mL; TEA LEAF OIL 0.0001 mL/100 mL; CREATININE 0.000000005 mL/100 mL; WATER 72.99113717364 mL/100 mL; BUTYLENE GLYCOL 6.80277 mL/100 mL; EDETATE DISODIUM ANHYDROUS 0.0200002 mL/100 mL; ECHINACEA PURPUREA WHOLE 0.00175 mL/100 mL; PERILLA FRUTESCENS LEAF 0.00175 mL/100 mL; XYLITOL 0.0012 mL/100 mL; SANDALWOOD OIL 0.0004375 mL/100 mL; CYSTEINE 0.00001150076 mL/100 mL; HYDROGENATED SOYBEAN LECITHIN 0.00001 mL/100 mL; CYCLOMETHICONE 5 0.09 mL/100 mL; DIBASIC POTASSIUM PHOSPHATE 0.00000000916 mL/100 mL; ALANINE 0.000044092 mL/100 mL; BLETILLA STRIATA TUBER 0.00175 mL/100 mL; ASPARTIC ACID 0.00007901456 mL/100 mL; PENTYLENE GLYCOL 0.00005 mL/100 mL; LYSINE 0.00004205828 mL/100 mL; ACETYL HEXAPEPTIDE-8 0.00000001 mL/100 mL; TRYPTOPHAN 0.0000000024 mL/100 mL; AMMONIA 0.000000001 mL/100 mL; CERAMIDE NP 0.000005 mL/100 mL; COPTIS JAPONICA ROOT 0.044115 mL/100 mL; HISTIDINE 0.000015018 mL/100 mL; POLYGLYCERYL-10 OLEATE 0.00001 mL/100 mL; LEVOCARNITINE HYDROCHLORIDE 0.000001 mL/100 mL; THIAMINE HYDROCHLORIDE 0.000001 mL/100 mL; TOCOPHEROL 0.000001 mL/100 mL; SODIUM LACTATE 0.0000002506 mL/100 mL; ORANGE OIL 0.025 mL/100 mL; HYALURONATE SODIUM 0.006 mL/100 mL; PELARGONIUM GRAVEOLENS FLOWER OIL 0.005375 mL/100 mL; PROPYLENE GLYCOL 0.0032 mL/100 mL; ANHYDROXYLITOL 0.0028 mL/100 mL; LAVENDER OIL 0.002625 mL/100 mL; LILIUM CANDIDUM BULB 0.002 mL/100 mL; SERINE 0.0001361992 mL/100 mL; DIMETHICONE/VINYL DIMETHICONE CROSSPOLYMER (HARD PARTICLE) 0.825 mL/100 mL; SAGE OIL 0.0005 mL/100 mL; NIACIN 0.000001 mL/100 mL; 1,2-HEXANEDIOL 0.404045 mL/100 mL; POGOSTEMON CABLIN LEAF OIL 0.000375 mL/100 mL; CHAMOMILE FLOWER OIL 0.00025 mL/100 mL; CARBOMER HOMOPOLYMER, UNSPECIFIED TYPE 0.3 mL/100 mL; PROPANEDIOL 6.735 mL/100 mL; TROMETHAMINE 0.22 mL/100 mL; GLUTAMIC ACID 0.00012610548 mL/100 mL; PANTOTHENIC ACID 0.000001 mL/100 mL

Ampoule

BANACOS Cica-aid Centella Peptide ampoule

METHIONINE

GLYCERIN

DIMETHICONE

stop use and ask a doctor

Take care not to get into the eye.

If you have any side effects such as red spots, swelling or tiching due to cosmetic or direct sunlight, consult your doctor.

PURPOSE

skinprotect

Warning

For external use only

Keep away from fire of flame

Do not spray on clothes because it can stain.

Be caeful not to get into your eyes, and if so wash thoroughly with water

Keep out of reach of children

indication

sprinkle evenly on your face

do not use in areas with wounds.
avoid eye contact

Direction

After cleansing in the morning and evening take an appropriate amount from the foundation makeup stage and spread it evenly over the face, neck, and other areas of your choice.

inactive

Glycereth-26
Dimethicone/Vinyl Dimethicone Crosspolymer
1,2-Hexanediol
Carbomer
Tromethamine
Chlorphenesin
Phenoxyethanol
Caprylyl Glycol
Ethylhexylglycerin
Cyclopentasiloxane
Cyclohexasiloxane
Benzophenone-5
Coptis Japonica Root Extract

Citrus Aurantium Dulcis (Orange) Peel Oil
Disodium EDTA
Melaleuca Alternifolia (Tea Tree) Leaf Water
Centella Asiatica Extract
Citrus Aurantium Dulcis (Orange) Oil
Citrus Aurantium Bergamia (Bergamot) Fruit Oil
Sodium Hyaluronate
Pelargonium Graveolens Flower Oil
Undaria Pinnatifida Extract

Echinacea Purpurea Extract
Perilla Ocymoides Leaf Extract
Bletilla Striata Root Extract
Xylitol
Sea Salt
Psidium Guajava Fruit Extract
Geranium Maculatum Oil
Salvia Officinalis (Sage) Oil
Santalum Album (Sandalwood) Oil
Glucose

Pogostemon Cablin Oil
Rose Flower Oil
Chamomilla Recutita (Matricaria) Flower Oil
Glycine
Serine
Glutamic Acid
Rosa Damascena Extract
Camellia Sinensis Leaf Water
Caprylic/Capric Triglyceride
Aspartic Acid
Leucine
Pentylene Glycol
Alanine
Lysine
Beta-Glucan
Arginine
Tyrosine
Phenylalanine
Threonine
Proline
Valine
Isoleucine
Phosphatidylcholine
Anthemis Nobilis Flower Water
Styrax Benzoin Gum
Commiphora Myrrha Oil
Histidine
Methionine
Cysteine
Hydrogenated Lecithin
Polyglyceryl-10 Oleate
Ceramide NP
Carnitine HCl
Thiamine HCl
Tocopherol
Niacin
Folic Acid
Retinyl Palmitate
Ascorbic Acid
Riboflavin
Biotin
Pantothenic Acid
Sodium Ascorbyl Phosphate
Magnesium PCA
Sodium Lactate
Copper Tripeptide-1
Sucrose
Urea
Calcium Chloride
Potassium Hydroxide
Ornithine
Magnesium Chloride
Palmitoyl Pentapeptide-4
Acetyl Hexapeptide-8
Palmitoyl Tripeptide-1
Dipotassium Phosphate
Magnesium Citrate
Glucosamine HCl
1-Methylhydantoin-2-Imide
Asparagine
Citrulline
Uric Acid
Taurine
Tryptophan
Formic Acid
Ammonia
Glutamine

label

79540-304-01